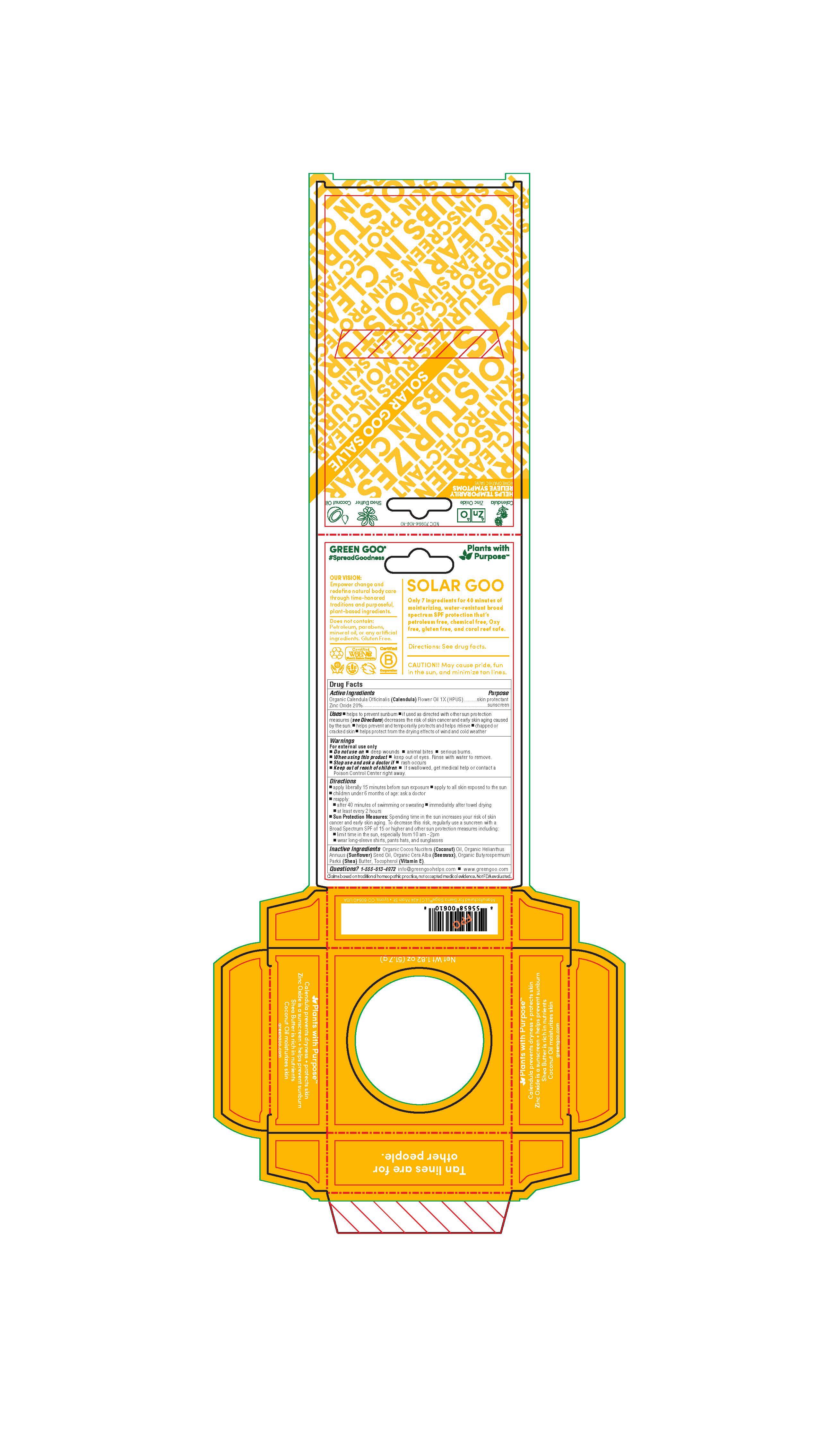 DRUG LABEL: Solar Goo
NDC: 70994-106 | Form: SALVE
Manufacturer: Spry Life LLC
Category: homeopathic | Type: HUMAN OTC DRUG LABEL
Date: 20231230

ACTIVE INGREDIENTS: ZINC OXIDE 18 g/113.4 g; CALENDULA OFFICINALIS FLOWER 1 [hp_X]/113.4 g
INACTIVE INGREDIENTS: SHEA BUTTER; YELLOW WAX; ALPHA-TOCOPHEROL; COCONUT OIL; SUNFLOWER OIL

Solar Goo

Purpose Section

Sunscreen

Skin Protectant

Active Ingredients

Zinc Oxide (Non-Nano) 20%
Organic Calendula Officinalis (Calendula) Flowers 1X (HPUS)

Indications & Usage

-helps to prevent sunburn • if used as directed with other sun
protection measures (see Directions) decrease the risk of skin cancer
and early skin aging caused by the sun.

Keep out of reach of children section

Keep out of reach of children. If this product is swallowed, get medical
help or contact a Poison Control Center right away.

Warnings Section

Warnings For external use only.
When using this product • avoid contact with eyes.

If contact occurs, rinse thoroughly with water. Stop use and ask a doctor if rash occurs

• Do not use on damaged or broken skin.

Storage

Store at room temperature.

Dosage & Administration Section

• Apply liberally 15 minutes before sun exposure
• reapply:
• after 40 minutes of swimming or sweating
• immediately after towel drying
• at least every 2 hours
•Sun Protection Measures. Spending time in the sun increases your
risk of skin cancer and early skin aging. To decrease this risk,
regularly use a suncream with a broad spectrum SPF of 15 or higher
and other sun protection measures including:
• limit time in the sun, especially from 10am -2pm
• wear long-sleeve shirts, pants, hats, and sunglasses
• children under 6 months: Ask a doctor

Inactive Ingredients

Beeswax (cera alba), Organic Cocos nucifera (Coconut) Oil, Organic Helianthus annus (Sunflower) Oil, Non-GMO (100% Sunflower) Mixed Tocopherols (Vitamin E), Butyrospermum parkii (Shea Butter).